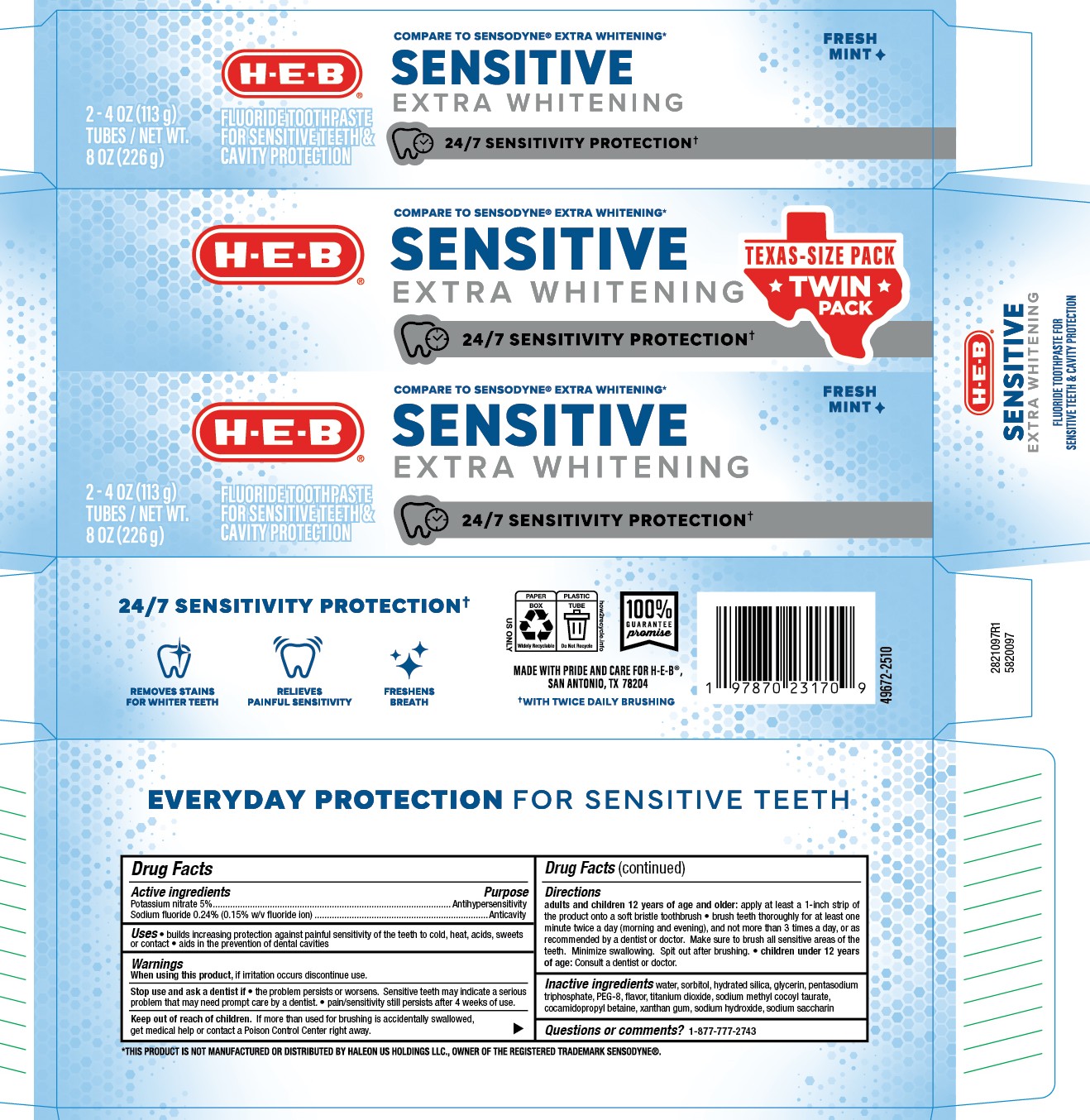 DRUG LABEL: HEB Sensitive Extra Whitening Twin
NDC: 37808-237 | Form: PASTE, DENTIFRICE
Manufacturer: HEB
Category: otc | Type: HUMAN OTC DRUG LABEL
Date: 20251208

ACTIVE INGREDIENTS: SODIUM FLUORIDE 0.15 g/100 g; POTASSIUM NITRATE 5 g/100 g
INACTIVE INGREDIENTS: WATER; PEG-8; GLYCERIN; HYDRATED SILICA; SODIUM SACCHARIN; TITANIUM DIOXIDE; SODIUM METHYL COCOYL TAURATE; XANTHAN GUM; SORBITOL; SODIUM HYDROXIDE; PENTASODIUM TRIPHOSPHATE; COCAMIDOPROPYL BETAINE

5820097 HEB Sensitive Extra Whitening Twinpack (8015201)

ACTIVE INGREDIENT

Potassium nitrate 5% ...................................................... Anthihypersensitivity

Sodium Fluoride 0.24% (0.15% w/v fluoride ion) .............Anticavity

PURPOSE

Antihypersensitivity

Anticavity

When using this product, if irritation occurs discontinue use.

When using this product, if irritation occurs discontinue use.

Stop use and ask a dentist if

- the problem persists or worsens. Sensitive teeth may indicate a serious problem that may need prompt care by a dentist.
- pain/sensitivity still persists after 4 weeks of use.

Keep out of reach of children. If more than used for brushing is accidentally swallowed, get medical help or contact a Poison Control Center right away.

DOSAGE AND ADMINISTRATION

Adults and children 12 years of age and older: apply at least a 1-inch strip of the product onto a soft bristle toothbrush

- brush teeth thoroughly for at least one minute twice a day (morning and evening), and not more than 3 times a day, or as recommended by a dentist or doctor. Make sure to brush all sensitive areas of the teeth. Minimize swallowing. Spit out after brushing.
- Children under 12 years of age: Consult a dentist or doctor.

INDICATIONS AND USAGE

Adults and children 12 years of age and older: apply at least a 1-inch strip of the product onto a soft bristle toothbrush

- brush teeth thoroughly for at least one minute twice a day (morning and evening), and not more than 3 times a day, or as recommended by a dentist or doctor. Make sure to brush all sensitive areas of the teeth. Minimize swallowing. Spit out after brushing.
- Children under 12 years of age: Consult a dentist or doctor.

INACTIVE INGREDIENT

water, sorbitol, hydrated silica, glycerin, pentasodium triphosphate, PEG-8, flavor, titanium dioxide, sodium methyl cocoyl taurate, cocamidopropyl betaine, xanthan gum, sodium hydroxide, sodium saccharin

Questions or comments? 1-877-777-2743